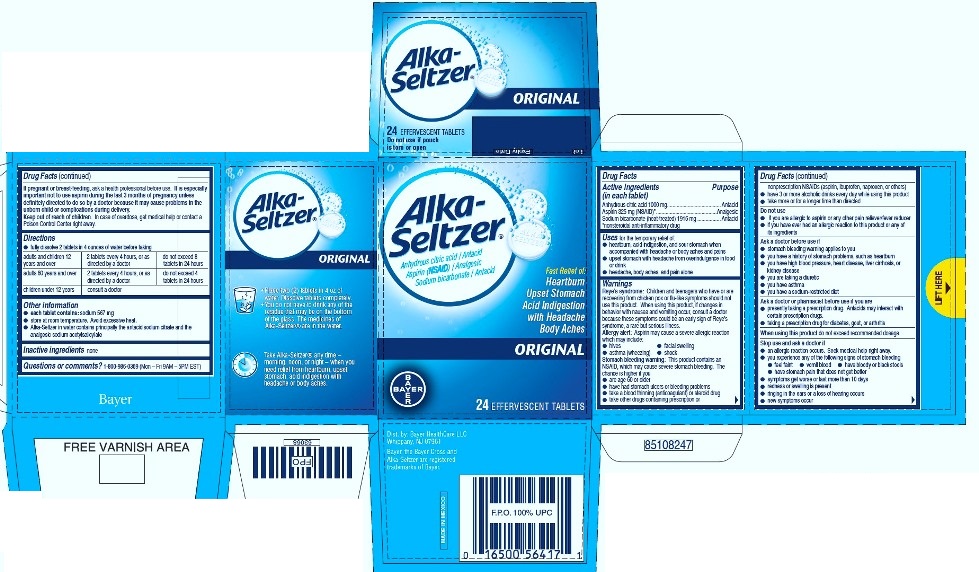 DRUG LABEL: Alka-Seltzer Original
NDC: 0280-4000 | Form: TABLET, EFFERVESCENT
Manufacturer: Bayer HealthCare LLC.
Category: otc | Type: HUMAN OTC DRUG LABEL
Date: 20251204

ACTIVE INGREDIENTS: ANHYDROUS CITRIC ACID 1000 mg/1 1; ASPIRIN 325 mg/1 1; SODIUM BICARBONATE 1916 mg/1 1

Alka-Seltzer® Original

Drug Facts

ACTIVE INGREDIENT

Active ingredients (in each tablet) | Purpose
Anhydrous citric acid 1000 mg | Antacid
Aspirin 325 mg (NSAID) [nonsteroidal anti-inflammatory drug] | Analgesic
Sodium bicarbonate (heat-treated) 1916 mg | Antacid

Uses

for the temporary relief of:

- heartburn, acid indigestion, and sour stomach when accompanied with headache or body aches and pains
- upset stomach with headache from overindulgence in food or drink
- headache, body aches, and pain alone

Warnings

Reye's syndrome

Children and teenagers who have or are recovering from chicken pox or flu-like symptoms should not use this product. When using this product, if changes in behavior with nausea and vomiting occur, consult a doctor because these symptoms could be an early sign of Reye's syndrome, a rare but serious illness.

Allergy alert

Aspirin may cause a severe allergic reaction which may include:

- hives
- facial swelling
- asthma (wheezing)
- shock

Stomach bleeding warning

This product contains an NSAID, which may cause severe stomach bleeding. The chance is higher if you

- are age 60 or older
- have had stomach ulcers or bleeding problems
- take a blood thinning (anticoagulant) or steroid drug
- take other drugs containing prescription or nonprescription NSAIDs (aspirin, ibuprofen, naproxen, or others)
- have 3 or more alcoholic drinks every day while using this product
- take more or for a longer time than directed

Do not use

- if you are allergic to aspirin or any other pain reliever/fever reducer
- if you have ever had an allergic reaction to this product or any of its ingredients

Ask a doctor before use if

- stomach bleeding warning applies to you
- you have a history of stomach problems, such as heartburn
- you have high blood pressure, heart disease, liver cirrhosis, or kidney disease
- you are taking a diuretic
- you have asthma
- you have a sodium-restricted diet

Ask a doctor or pharmacist before use if you are

- presently taking a prescription drug. Antacids may interact with certain prescription drugs.
- taking a prescription drug for diabetes, gout, or arthritis

When using this product do not exceed recommended dosage

Stop use and ask a doctor if

- an allergic reaction occurs. Seek medical help right away.
- you experience any of the following signs of stomach bleeding
  - feel faint
  - vomit blood
  - have bloody or black stools
  - have stomach pain that does not get better
- symptoms get worse or last more than 10 days
- redness or swelling is present
- ringing in the ears or a loss of hearing occurs
- new symptoms occur

PREGNANCY OR BREAST FEEDING

If pregnant or breast-feeding, ask a health professional before use. It is especially important not to use aspirin during the last 3 months of pregnancy unless definitely directed to do so by a doctor because it may cause problems in the unborn child or complications during delivery.

Keep out of reach of children. In case of overdose, get medical help or contact a Poison Control Center right away.

Directions

● fully dissolve 2 tablets in 4 ounces of water before taking

adults and children 12 years and over | 2 tablets every 4 hours, or as directed by a doctor | do not exceed 8 tablets in 24 hours
adults 60 years and over | 2 tablets every 4 hours, or as directed by a doctor | do not exceed 4 tablets in 24 hours
children under 12 years | consult a doctor

Other information

- each tablet contains: sodium 567 mg
- store at room temperature. Avoid excessive heat.
- Alka-Seltzer in water contains principally the antacid sodium citrate and the analgesic sodium acetylsalicylate

Inactive ingredients

none

Questions or comments?

1-800-986-0369 (Mon – Fri 9AM – 5PM EST)

Dist. by: Bayer HealthCare LLC
Whippany, NJ 07981

PRINCIPAL DISPLAY PANEL - 24 Tablet Carton

Alka-
Seltzer®

Anhydrous citric acid / Antacid
Aspirin (NSAID) / Analgesic
Sodium bicarbonate / Antacid

Fast Relief of:
Heartburn
Upset Stomach
Acid Indigestion
with Headache
Body Aches

ORIGINAL

24 EFFERVESCENT TABLETS